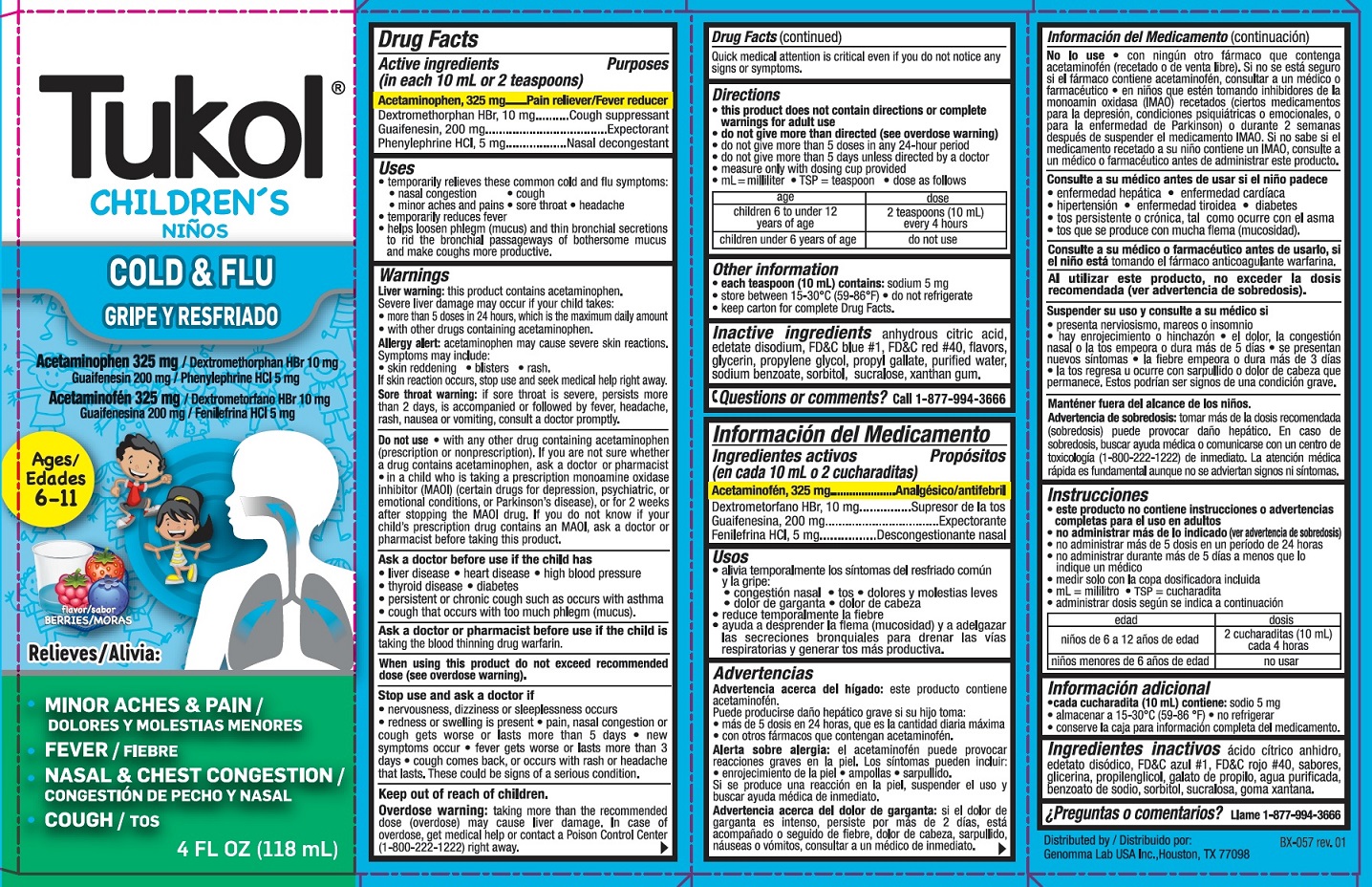 DRUG LABEL: Childrens Tukol Multi-Symptom Cold and Flu
NDC: 50066-519 | Form: LIQUID
Manufacturer: Genomma Lab USA, Inc.
Category: otc | Type: HUMAN OTC DRUG LABEL
Date: 20240111

ACTIVE INGREDIENTS: ACETAMINOPHEN 325 mg/10 mL; DEXTROMETHORPHAN HYDROBROMIDE 10 mg/10 mL; GUAIFENESIN 200 mg/10 mL; PHENYLEPHRINE HYDROCHLORIDE 5 mg/10 mL
INACTIVE INGREDIENTS: ANHYDROUS CITRIC ACID; EDETATE DISODIUM; FD&C BLUE NO. 1; FD&C RED NO. 40; GLYCERIN; PROPYLENE GLYCOL; PROPYL GALLATE; WATER; SODIUM BENZOATE; SORBITOL; SUCRALOSE; XANTHAN GUM

Children's Tukol Multi-Symptom Cold & Flu 519

Drug Facts Active ingredients (in each 10 mL = 2 teaspoonful)

Acetaminophen 325 mg
Dextromethorphan HBr 10 mg
Guaifenesin 200 mg
Phenylephrine HCL 5 mg

Purpose

Pain reliever/fever reducer
Cough suppressant
Expectorant
Nasal decongestant

Uses

temporarily relieves these common cold and flu symptoms:

- nasal congestion
- cough
- minor aches and pains
- sore throat
- headache
- temporarily reduces fever
- helps loosen phlegm (mucus) and thin bronchial secretions to rid the bronchial passageways of bothersome mucus and make coughs more productive

Warnings

Liver warning: This product cantains acetaminophen. Severe liver damage may occur if your child takes

- more tha 5 doses in 24 hours which is the maxium daily amount
- with other drugs containing acetaminophen

Allergy alert: Acetaminophen may cause severe skin reactions. Symptoms may include:

- skin reddening
- blisters
- rash

If skin reaction occurs, stop use and seek medical help right away.

Sore throat warning: if sore throat is severe, persists more than 2 days, is accompanied or followed by fever, headache, rash, nausea or vomitting, consult a doctor promptly.

Do not use

- with any other drug containing acetaminophen (prescription or non prescription). If you are not sure whether a drug containd acetaminophen, ask a doctor or pharmacist
- for a child who is taking a prescription monoamine oxidase inhibitor (MAOI) (certain drugs for depression, psychiatric, or emotional conditions, or Parkinson's disease). or for 2 weeks after stopping an MAOI drug. If you do not know if ask a doctor or pharmacist beforre giving this product.

Ask a doctor before use if the child has

- liver disease
- heart disease
- high blood pressure
- thyroid disease
- diabetes
- persistant or chronic cough such as occurs with asthma
- cough that occurs with too much phlegm (musus)

Ask a doctor or pharmacist before use if the child is

taking the blood thinning drug warfarin.

When using this product

- do not exceed recommended dose (see overdose section).

Stop use and ask a doctor if

- nervousness, dizziness or sleeplessness occur
- redness or swelling is present
- pain, nasal congestion or cough gets worse or lasts more than 5 days
- new symptoms occur
- fever gets worse or lasts more than 3 days
- cough comes back, or occurs with rash or headache that lasts

These could be signs of a serious condition.

Keep out of reach of children.

Overdose warning

Taking more than the recommended dose (overdose) may cause liver damage.

In case of overdose, get medical help or contact a Poison Control Center (1-800-222-1222) right away.
Quick medical attentioni is critical even if you do not notice any signs or symptoms.

Directions

- this product does not contain directions or complete warning for adult use
- do not give more than directed
  (see Overdose warning)
- do not give more than 5 doses in any 24-hour period
- do not give for more than 5 days unless directed by a doctor
- measure only with dosing cup provided
- dose as follows or as directed by a doctor
- mL = milliliter; TSP = teaspoon
- dose as follows

age | dose
children 6 to under 12 years of age | 2 teaspoons (10 mL) every 4 hours
children under 6 years of age | do not use

Other information

- each teaspoon 10 mL contains: sodium 5 mg
- store between 15-30°C (59-86°F)
- do not refrigerate
- keep carton for complete Drug facts

Inactive ingredients

anhydrous citric acid, edetate disodium, FD&C Blue #1, FD&C Red # 40, flavors, glycerin, propylene glycol, propyl gallate, purified water, sodium benzoate, orbitol, sucralsoe, xanthan gum

Questions?

Call 1-877-994-3666

Children's Tukol Multi-Symptom Cold & Flu product label

KEEP CARTON FOR COMPLETE DRUG FACTS

DO NOT USE IF PRINTED SEAL UNDER CAP IS TORN OR MISSING

Tukol®

Childrens

COLD & FLU

Acetaminophen 325 mg/Dextromethorphan HBr 10 mg/Guaifenesin 200 mg/Phenylephrine HCL 5 mg

Ages 6-11

Relieves

Minor Aches & Pain

Fever

Nasal & Chest Congestion

4 FL OZ (118 mL)

Distributed By
Genomma Lab USA Inc. Houston, TX 77098